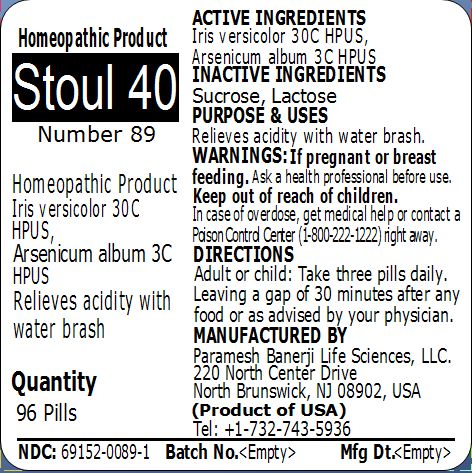 DRUG LABEL: Stoul 40 (Number 89)
NDC: 69152-0089 | Form: PELLET
Manufacturer: Paramesh Banerji Life Sciences LLC
Category: homeopathic | Type: HUMAN OTC DRUG LABEL
Date: 20150309

ACTIVE INGREDIENTS: IRIS VERSICOLOR ROOT 30 [hp_C]/1 1; ARSENIC TRIOXIDE 3 [hp_C]/1 1
INACTIVE INGREDIENTS: SUCROSE; LACTOSE

Active Ingredients

Iris versicolor 30C HPUS, Arsenicum album 3C HPUS

Inactive Ingredients

Sucrose, Lactose

Purpose

Relieves acidity with water brash

Uses

Relieves acidity with water brash

Warnings

If pregnant or breast feeding ask a health professional before use.

Keep out of reach of children. In case of overdose, get medical help or contact a Poison Control Center (1-800-222-1222) right away.

Direction

Adult or child: Take three pills daily. Leaving a gap of 30 minutes after any food or as advised by your physician.

Manufactured by

Paramesh Banerji Life Sciences, LLC

220 North Center Drive

North Brunswick, NJ 08902, USA

Product of USA

Tel: +1-732-743-5936

Principal Display Panel

Homeopathic Product

Stoul 40

Number 89

Homeopathic Product

Iris versicolor 30C HPUS, Arsenicum album 3C HPUS

Relieves acidity with water brash

Quantity

96 Pills